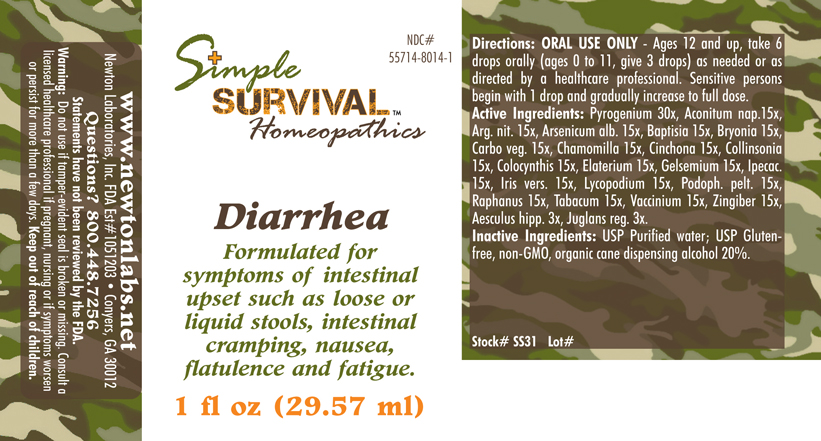 DRUG LABEL: Diarrhea 
NDC: 55714-8014 | Form: LIQUID
Manufacturer: Newton Laboratories, Inc.
Category: homeopathic | Type: HUMAN OTC DRUG LABEL
Date: 20140415

ACTIVE INGREDIENTS: Rancid Beef 30 [hp_X]/1 mL; Aconitum Napellus 15 [hp_X]/1 mL; Silver Nitrate 15 [hp_X]/1 mL; Arsenic Trioxide 15 [hp_X]/1 mL; Baptisia Tinctoria 15 [hp_X]/1 mL; Bryonia Alba Root 15 [hp_X]/1 mL; Activated Charcoal 15 [hp_X]/1 mL; Matricaria Recutita 15 [hp_X]/1 mL; Cinchona Officinalis Bark 15 [hp_X]/1 mL; Collinsonia Canadensis Root 15 [hp_X]/1 mL; Citrullus Colocynthis Fruit Pulp 15 [hp_X]/1 mL; Ecballium Elaterium Fruit 15 [hp_X]/1 mL; Gelsemium Sempervirens Root 15 [hp_X]/1 mL; Ipecac 15 [hp_X]/1 mL; Iris Versicolor Root 15 [hp_X]/1 mL; Lycopodium Clavatum Spore 15 [hp_X]/1 mL; Podophyllum 15 [hp_X]/1 mL; Radish 15 [hp_X]/1 mL; Tobacco Leaf 15 [hp_X]/1 mL; Bilberry 15 [hp_X]/1 mL; Ginger 15 [hp_X]/1 mL; Horse Chestnut 3 [hp_X]/1 mL; English Walnut 3 [hp_X]/1 mL
INACTIVE INGREDIENTS: Alcohol

Diarrhea

INDICATIONS & USAGE SECTION

Diarrhea Formulated for symptoms of intestinal upset such as loose or liquid stools, intestinal cramping, nausea, flatulence and fatigue.

DOSAGE & ADMINISTRATION SECTION

Directions: ORAL USE ONLY - Ages 12 and up, take 6 drops orally (ages 0 to 11, give 3 drops) as needed or as directed by a healthcare professional. Sensitive persons begin with 1 drop and gradually increase to full dose.

OTC - ACTIVE INGREDIENT SECTION

Pyrogenium 30x, Aconitum nap.15x, Arg. nit. 15x, Arsenicum alb. 15x, Baptisia 15x, Bryonia 15x, Carbo veg. 15x, Chamomilla 15x, Cinchona 15x, Collinsonia 15x, Colocynthis 15x, Elaterium 15x, Gelsemium 15x, Ipecac. 15x, Iris vers. 15x, Lycopodium 15x, Podoph. pelt. 15x, Raphanus 15x,Tabacum 15x, Vaccinium 15x, Zingiber 15x, Aesculus hipp. 3x, Juglans reg. 3x.

OTC - PURPOSE SECTION

Formulated for symptoms of intestinal upset such as loose or liquid stools, intestinal cramping, nausea, flatulence and fatigue.

INACTIVE INGREDIENT SECTION

Inactive Ingredients: USP Purified Water; USP Gluten-free, non-GMO, organic cane dispensing alcohol 20%.

QUESTIONS SECTION

www.newtonlabs.net Newton Laboratories, Inc. FDA Est # 1051203 - Conyers, GA 30012
Questions? 1.800.448.7256

WARNINGS SECTION

Warning: Do not use if tamper - evident seal is broken or missing. Consult a licensed healthcare professional if pregnant, nursing or if symptoms worsen or persist for more than a few days. Keep out of reach of children.

OTC - PREGNANCY OR BREAST FEEDING SECTION

Consult a licensed healthcare professional if pregnant, nursing or if symptoms worsen or persist for more than a few days.

OTC - KEEP OUT OF REACH OF CHILDREN SECTION

Keep out of reach of children.